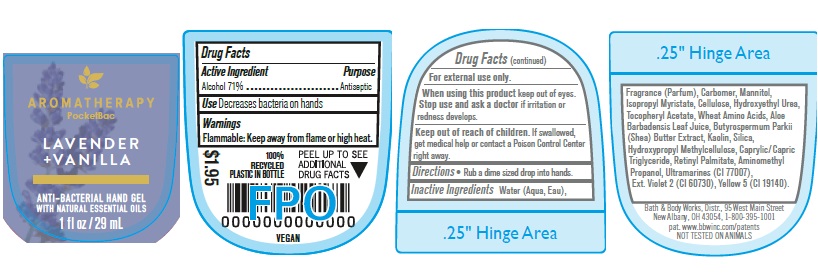 DRUG LABEL: Anti Bacterial Hand Gel
NDC: 62670-6768 | Form: GEL
Manufacturer: Bath & Body Works, Inc.
Category: otc | Type: HUMAN OTC DRUG LABEL
Date: 20260302

ACTIVE INGREDIENTS: ALCOHOL 71 mL/100 mL
INACTIVE INGREDIENTS: WATER

ABHG Lavender and Vanilla

Active Ingredient

Alcohol 71%

Purpose

Antiseptic

Use

Decreases bacteria on hands.

Warnings

Flammable: Keep away from flame or high heat.

WARNINGS

For external use only.

When using this product keep out of eyes. Stop use and ask a doctor if irritation or redness develops.

Keep out of reach of children. If swallowed, get medical help or contact a Poison Control Center right away.

Directions

Rub a dime sized drop into hands.

INACTIVE INGREDIENT

Water (Aqua, Eau), Fragrance (Parfum), Carbomer, Mannitol, Isopropyl Myristate, Cellulose, Hydroxyethyl Urea, Tocopheryl Acetate, Wheat Amino Acids, Aloe Barbadensis Leaf Juice, Butyrospermum Parkii (Shea) Butter Extract, Kaolin, Silica, Hydroxypropyl Methylcellulose, Caprylic/Capric Triglyceride, Retinyl Palmitate, Aminomethyl Propanol, Ultramarines (CI 77007), Ext. Violet 2 (CI 60730), Yellow 5 (CI 19140).

Bath & Body Works, Distr., 95 West Main Street
New Albany, OH 43054, 1-800-395-1001
pat. www.bbwinc.com/patents